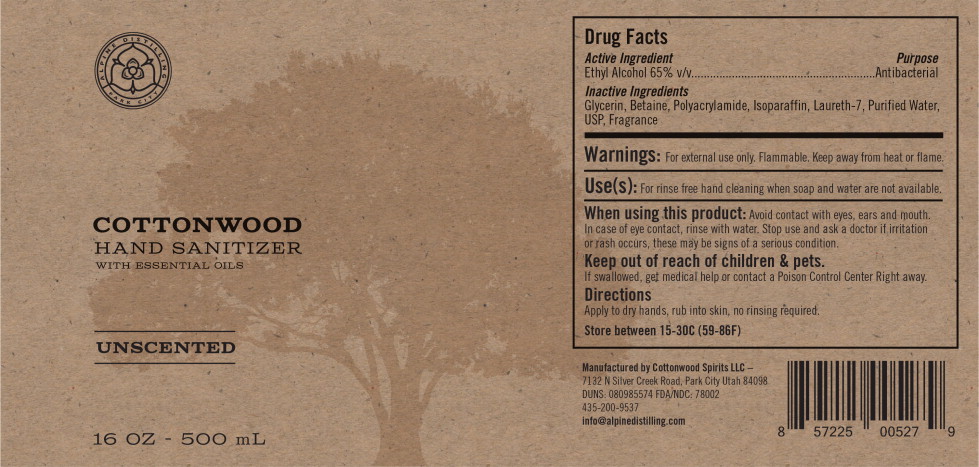 DRUG LABEL: Cottonwood Sanitizer 
NDC: 78002-101 | Form: GEL
Manufacturer: Alpine Distilling
Category: otc | Type: HUMAN OTC DRUG LABEL
Date: 20200706

ACTIVE INGREDIENTS: ALCOHOL 65 mL/100 mL
INACTIVE INGREDIENTS: Glycerin; Betaine; Polyacrylamide (Crosslinked; 0.01-0.2 Mole Percent Bisacrylamide); C13-14 ISOPARAFFIN; Laureth-7; Water

Drug Facts

Active Ingredient(s):

Ethyl Alcohol 65% v/v

Purpose :

Antibacterial

Use(s):

For rinse free hand cleaning when soap and water are not available.

Warning:

For external use only. Flammable. Keep away from heat or flame.

When using this product: Avoid contact with eyes, ears and mouth. In case of eye contact, rinse with water. Stop use and ask a doctor if irritation or rash occurs, these may be signs of a serious condition.

Keep out of reach of children & pets. If swallowed, get medical help or contact a Poison Control Center Right away.

Directions:

Apply to dry hands, rub into skin, no rinsing required.

Other Information:

Store between 15-30C (59-86F)

Inactive Ingredients:

Glycerin, Betaine, Polyacrylamide, Isoparaffin, Laureth-7, Purified Water USP, Fragrance

Manufactured by Cottonwood Spirits LLC – 7132 N Silver Creek Road, Park City Utah 84098

DUNS: 080985574 FDA/NDC: 78002

435-200-9537 info@alpinedistilling.com

Principal Display Panel – 500 mL Bottle Label

COTTONWOORD
HAND SANITIZER
WITH ESSENTIAL OILS

UNSCENTED

16 OZ – 500 mL